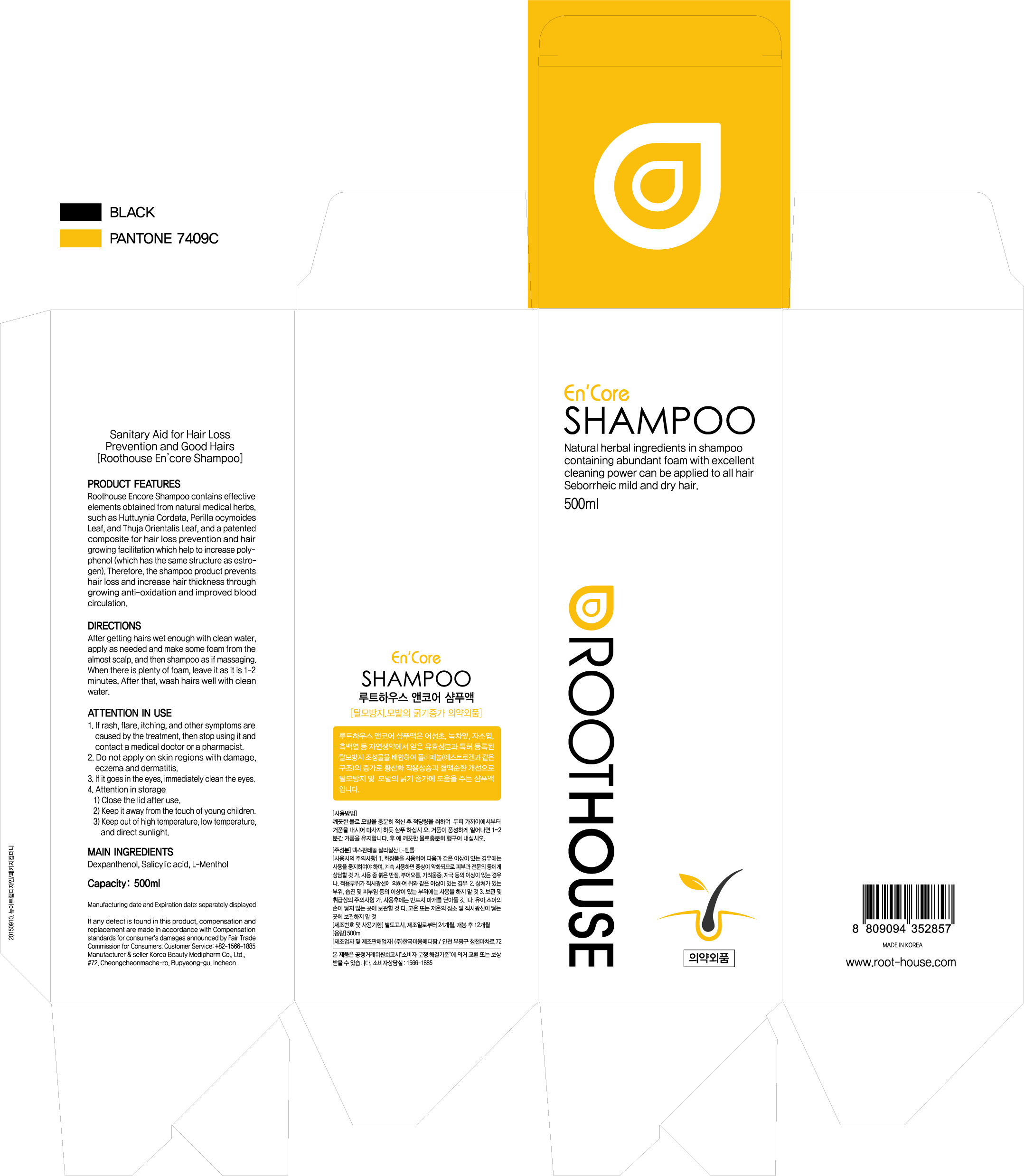 DRUG LABEL: Roothouse EnCore
NDC: 70652-0001 | Form: SHAMPOO
Manufacturer: Roothouse
Category: otc | Type: HUMAN OTC DRUG LABEL
Date: 20160426

ACTIVE INGREDIENTS: SALICYLIC ACID 0.25 g/100 mL
INACTIVE INGREDIENTS: PERILLA FRUTESCENS LEAF; DEXPANTHENOL; WATER; DIMETHICONE; PLATYCLADUS ORIENTALIS LEAF

Drug Facts

ACTIVE INGREDIENT

Salicylic Acid, Dexpanthenol, L-Menthol

INACTIVE INGREDIENT

Water, Dimethicone, Perilla Frutescens Leaf (Perilla Ocymoides Leaf), and Thuja Orientalis Leaf, etc.

PURPOSE

Prevent hair loss and increase hair thickness.

Keep out or reach of the children

INDICATIONS AND USAGE

After getting hairs wet enough with clean water, apply as needed and make some foam from the almost scalp, and then shampoo as if massaging. When there is plenty of foam, leave it as it is 1-2 minutes. After that, wash hairs well with clean water.

WARNINGS

1. If rash, flare, itching, and other symptoms are caused by the treatment, then stop using it and contact a medical doctor or a pharmacist.
2. Do not apply on skin regions with damage, eczema and dermatitis.
3. If it goes in the eyes, immediately clean the eyes.
4. Attention in storage

1) Close the lid after use.

2) Keep it away from the touch of young children.

3) Keep out of high temperature, low temperature, and direct sunlight.

DOSAGE AND ADMINISTRATION

For external use only